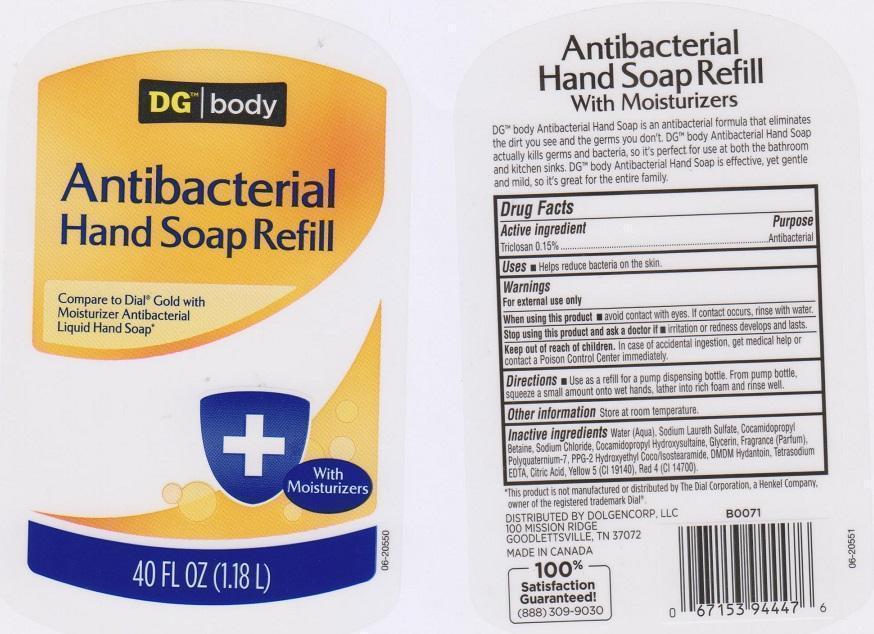 DRUG LABEL: DG BODY
NDC: 55910-294 | Form: SOAP
Manufacturer: DOLGENCORP INC
Category: otc | Type: HUMAN OTC DRUG LABEL
Date: 20150617

ACTIVE INGREDIENTS: TRICLOSAN 1.5 mg/1 mL
INACTIVE INGREDIENTS: WATER; SODIUM LAURETH SULFATE; COCAMIDOPROPYL BETAINE; SODIUM CHLORIDE; COCAMIDOPROPYL HYDROXYSULTAINE; GLYCERIN; POLYQUATERNIUM-7 (70/30 ACRYLAMIDE/DADMAC; 1600000 MW); PPG-2 HYDROXYETHYL COCO/ISOSTEARAMIDE; DMDM HYDANTOIN; EDETATE SODIUM; CITRIC ACID MONOHYDRATE; FD&C YELLOW NO. 5; FD&C RED NO. 4

DRUG FACTS

ACTIVE INGREDIENT

TRICLOSAN 0.15%

PURPOSE

ANTIBACTERIAL

USES

HELPS REDUCE BACTERIA ON THE SKIN

WARNINGS

FOR EXTERNAL USE ONLY

WHEN USING THIS PRODUCT

AVOID CONTACT WITH EYES. IF CONTACT OCCURS, RINSE WITH WATER

STOP USING THIS PRODUCT AND ASK A DOCTOR IF

IRRITATION OR REDNESS DEVELOPS AND LASTS

KEEP OUT OF REACH OF CHILDREN

IN CASE OF ACCIDENTAL INGESTION, GET MEDICAL HELP OR CONTACT A POISON CONTROL CENTER IMMEDIATELY

DIRECTIONS

USE AS A REFILL FOR A PUMP DISPENSING BOTTLE. FROM PUMP BOTTLE, SQUEEZE A SMALL AMOUNT ONTO WET HANDS, LATHER INTO RICH FOAM AND RINSE WELL

OTHER INFORMATION

STORE AT ROOM TEMPERATURE

INACTIVE INGREDIENTS

WATER (AQUA), SODIUM LAURETH SULFATE, COCAMIDOPROPYL BETAINE, SODIUM CHLORIDE, COCOAMIDOPROPYL HYDROXYSULTAINE, GLYCERIN, FRAGRANCE (PARFUM), POLYQUATERNIUM-7, PPG-2 HYDROXYETHYL COCO/ISOSTEARAMIDE, DMDM HYDANTOIN, TETRASODIUM EDTA, CITRIC ACID, YELLOW 5 (CI 19140), RED 4 (CI 14700)